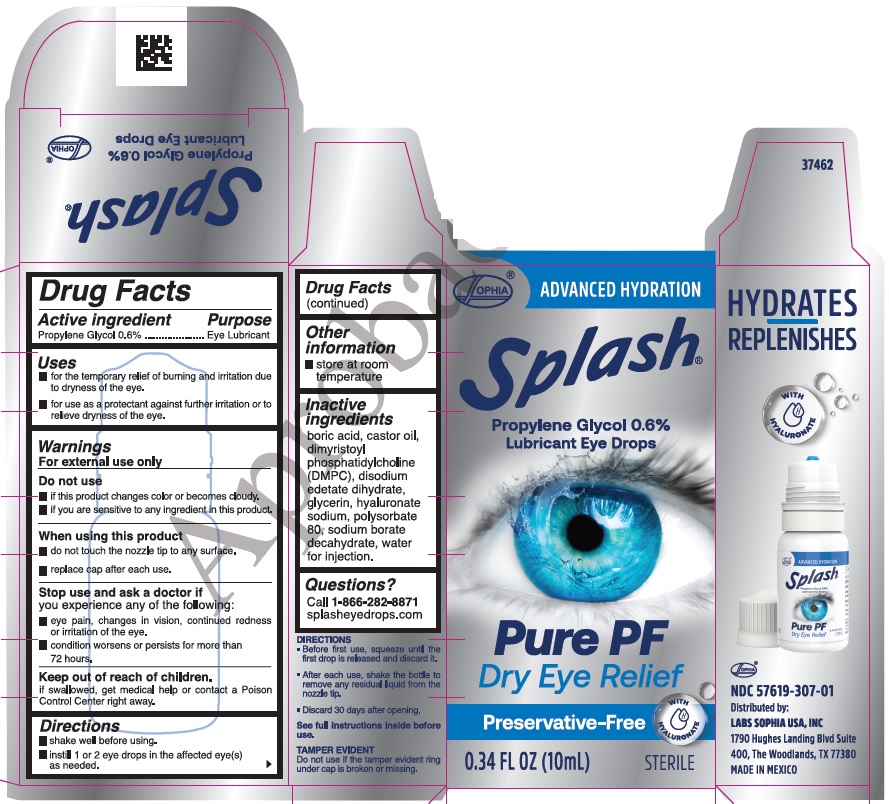 DRUG LABEL: Splash Pure PF
NDC: 57619-307 | Form: EMULSION
Manufacturer: LABORATORIOS SOPHIA, S.A. DE C.V.
Category: otc | Type: HUMAN OTC DRUG LABEL
Date: 20251126

ACTIVE INGREDIENTS: PROPYLENE GLYCOL 6 mg/1 mL
INACTIVE INGREDIENTS: POLYSORBATE 80; HYALURONATE SODIUM; WATER; CASTOR OIL; EDETATE DISODIUM; GLYCERIN; BORIC ACID; SODIUM BORATE; DIMYRISTOYLPHOSPHATIDYLCHOLINE, DL-

Splash

Active ingredient

Propylene Glycol 0.6%

Purpose

Eye Lubricant

Uses

- for the temporary relief of burning and irritation due to dryness of the eye.
- for use as a protectant against further irritation or to relieve dryness of the eye.

Warnings

For external use only

Do not use

- if this product changes color or becomes cloudy.
- if you are sensitive to any ingredient in this product.

When using this product

- do not touch the nozzle tip to any surface.
- replace cap after each use.

Stop use and ask a dotor if

- eye pain, changes in vision, continued redness or irritation of the eye.
- condition worsens or persists for more than 72 hours.

Keep out of reach of children.

if swallowed, get medical help or contact a Poison Control Center right away.

Directions

- shake well before using.
- instill 1 or 2 eye drops in the affected eye(s) as needed.

Other information

store at room temperature

Inactive ingredients
boric acid, castor oil, dimyristoyl phosphatidylcholine (DMPC), disodium edetate dihydrate, glycerin, hyaluronate sodium, polysorbate 80, sodium borate decahydrate, water for injection.

Questions?
Call 1-866-282-8871
splasheyedrops.com

HYDRATES

REPLENISHES

NDC 57619-307-01
Distributed by:
LABS SOPHIA USA, INC
1790 Hughes Landing Blvd Suite
400, The Woodlands, TX 77380
MADE IN MEXICO

DIRECTIONS
▪ Before first use, squeeze until the first drop is released and discard it.
▪ After each use, shake the bottle to remove any residual liquid from the nozzle tip.
▪ Discard 30 days after opening.
See full instructions inside before use.
TAMPER EVIDENT
Do not use if the tamper evident ring under cap is broken or missing.

PACKAGE LABEL

SOPHIA®

ADVANCED HYDRATION

Splash®

Propylene Glycol 0.6%

Lubricant Eye Drops

PURE PF

Dry Eye Relief

Preservative-Free

0.34 FL OZ (10mL) STERILE